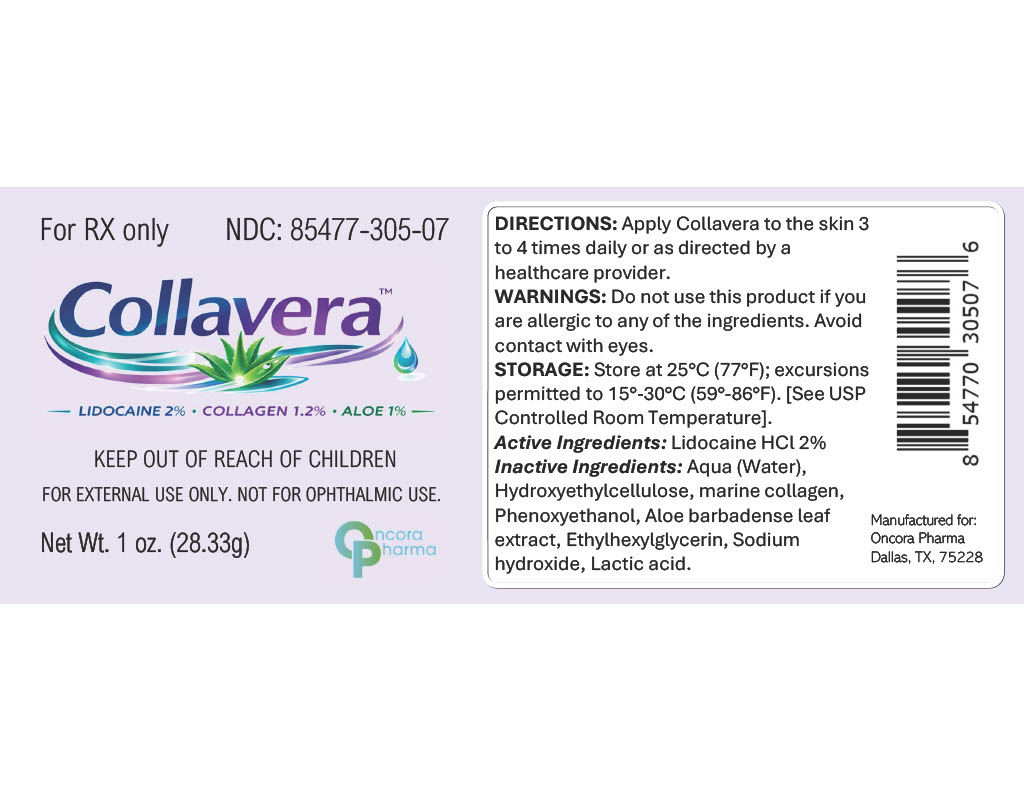 DRUG LABEL: Collavera
NDC: 85477-305 | Form: GEL
Manufacturer: Oncora Pharma, LLC
Category: prescription | Type: HUMAN PRESCRIPTION DRUG LABEL
Date: 20260227

ACTIVE INGREDIENTS: LIDOCAINE 20 mg/1 g
INACTIVE INGREDIENTS: WATER; HYDROXYETHYLCELLULOSE; MARINE COLLAGEN, SOLUBLE; PHENOXYETHANOL; ALOE BARBADENSIS LEAF; ETHYLHEXYLGLYCERIN; SODIUM HYDROXIDE; LACTIC ACID

Collavera™ (Lidocaine Hydrochloride) Topical Gel

DESCRIPTION

Collavera™ contains Lidocaine Hydrochloride 20 mg/g (2%) in a topical gel base.

INDICATIONS AND USAGE

Collavera™ is indicated for topical analgesia as directed by a healthcare provider.

WARNINGS

For external use only. Not for ophthalmic use.
Avoid contact with eyes.
Excessive application may result in systemic absorption. Use only as directed.
Keep out of reach of children.

OVERDOSAGE

Excessive topical application may increase systemic absorption of lidocaine and may result in central nervous system and cardiovascular effects. In the event of overdose, discontinue use and seek medical attention.

DOSAGE AND ADMINISTRATION

For topical use only.
Apply a thin layer to the affected area 3 to 4 times daily or as directed by a healthcare provider.
Avoid contact with eyes and mucous membranes.

HOW SUPPLIED

Collavera™ (Lidocaine Hydrochloride 20 mg/g) is supplied as a clear topical gel in a 1 oz (28.33 g) tube.
NDC 85477-305-07

PRINCIPAL DISPLAY PANEL

pdp